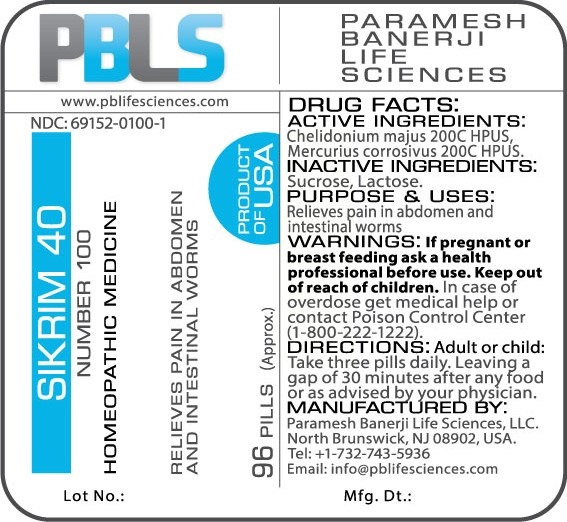 DRUG LABEL: Sikrim 40 Number 100
NDC: 69152-0100 | Form: PELLET
Manufacturer: Paramesh Banerji Life Sciences LLC
Category: homeopathic | Type: HUMAN OTC DRUG LABEL
Date: 20170717

ACTIVE INGREDIENTS: MERCURIC CHLORIDE 200 [hp_C]/1 1; CHELIDONIUM MAJUS 200 [hp_C]/1 1
INACTIVE INGREDIENTS: SUCROSE; LACTOSE

DRUG FACTS: Active Ingredients

Chelidonium majus 200C HPUS, Mercurius corrosivus 200C HPUS

Inactive Ingredients

Sucrose, Lactose

Purpose

Relieves pain in abdomen and intestinal worms

Uses

Relieves pain in abdomen and intestinal worms

Warnings

If pregnant or breast feeding ask a health professional before use.

Keep out of reach of children. In case of overdose, get medical help or contact a Poison Control Center (1-800-222-1222) right away.

Direction

Adult or child: Take three pills daily. Leaving a gap of 30 minutes after any food or as advised by your physician.

Manufactured by

Paramesh Banerji Life Sciences, LLC.

North Brunswick, NJ 08902, USA.

Tel: +1-732-743-5936

Email: info@pblifesciences.com

Principal Display Panel

NDC: 69152-0100-1

Sikrim 40

Number 100

Homeopathic Medicine

Relieves pain in abdomen and intestinal worms

96 Pills (Approx.)

Product of USA